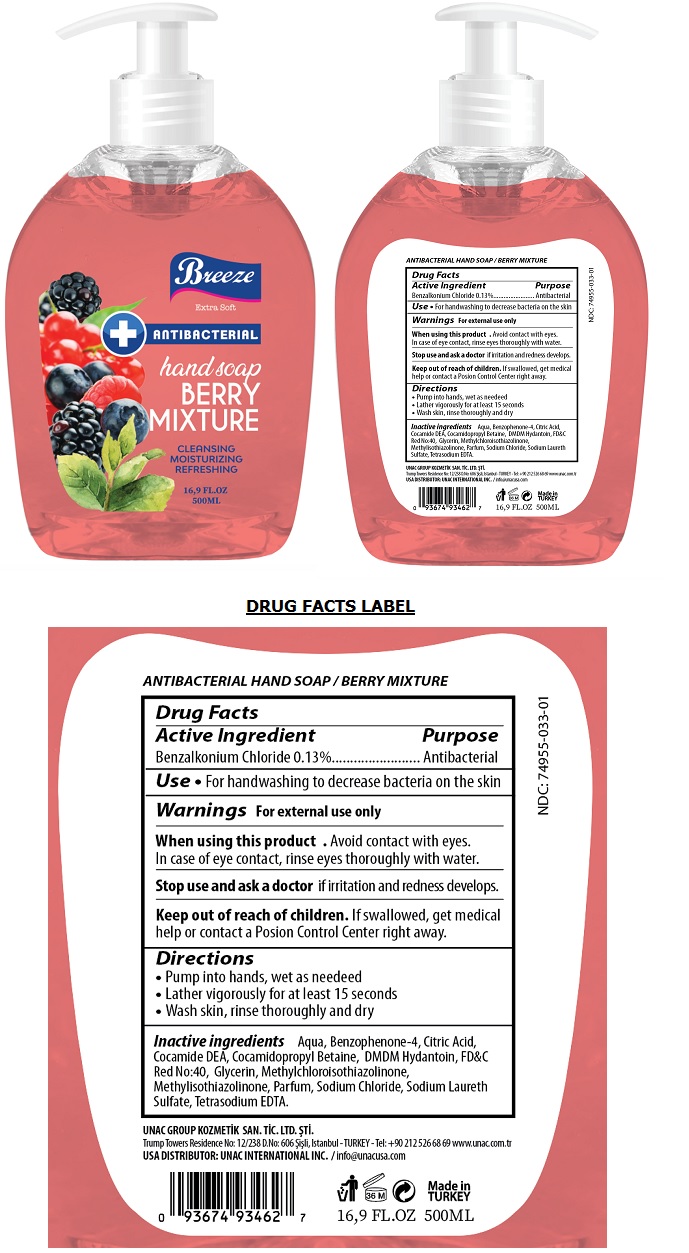 DRUG LABEL: BREEZE ANTIBACTERIAL HANDSOAP BERRY MIXTURE
NDC: 74955-033 | Form: LIQUID
Manufacturer: COSMOLIVE KOZMETIK SANAYI VE TICARET ANONIM SIRKETI
Category: otc | Type: HUMAN OTC DRUG LABEL
Date: 20201026

ACTIVE INGREDIENTS: BENZALKONIUM CHLORIDE 0.13 g/100 mL
INACTIVE INGREDIENTS: WATER; SULISOBENZONE; CITRIC ACID MONOHYDRATE; COCO DIETHANOLAMIDE; COCAMIDOPROPYL BETAINE; DMDM HYDANTOIN; FD&C RED NO. 40; GLYCERIN; METHYLCHLOROISOTHIAZOLINONE; METHYLISOTHIAZOLINONE; SODIUM CHLORIDE; SODIUM LAURETH-3 SULFATE; EDETATE SODIUM

Breeze ANTIBACTERIAL hand soap BERRY MIXTURE

Active Ingredient

Benzalkonium Chloride 0.13%

Purpose

Antibacterial

Use

• For handwashing to decrease bacteria on the skin

Warnings

For external use only

When using this product • Avoid contact with eyes. In case of eye contact, rinse eyes thoroughly with water.

Stop use and ask a doctor if irritation and redness develops.

Keep out of reach of children. If swallowed, get medical help or contact a Poison Control Center right away.

Directions

• Pump into hands, wet as needed

• Lather vigorously for at least 15 seconds

• Wash skin, rinse thoroughly and dry

Inactive ingredients

Aqua, Benzophenone-4, Citric Acid, Cocamide DEA, Cocamidopropyl Betaine, DMDM Hydantoin, FD&C Red No:40, Glycerin, Methylchloroisothiazolinone, Methylisothiazolinone, Parfum, Sodium Chloride, Sodium Laureth Sulfate, Tetrasodium EDTA.

Extra Soft

CLEANSING

MOISTURIZING

REFRESHING

UNAC GROUP KOZMETİK SAN. TİC. LTD. ŞTİ

Trump Towers Residence No: 12/238 D.No:606 Şişli, Istanbul- TURKEY - Tel: +90 212 526 68 69 www.unac.com.tr

USA DISTRIBUTOR: UNAC INTERNATIONAL INC. / info@unacusa.com

Made in TURKEY